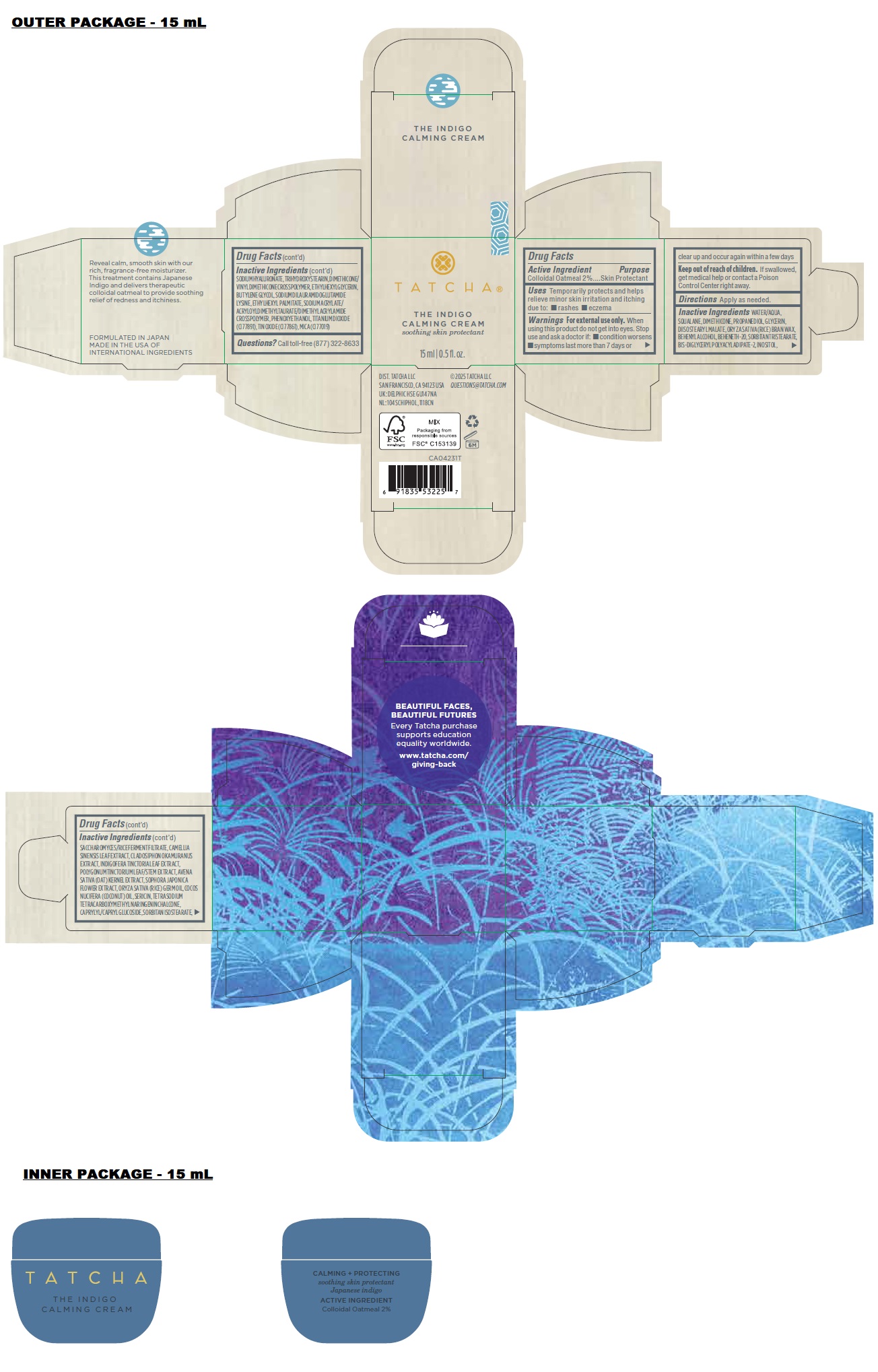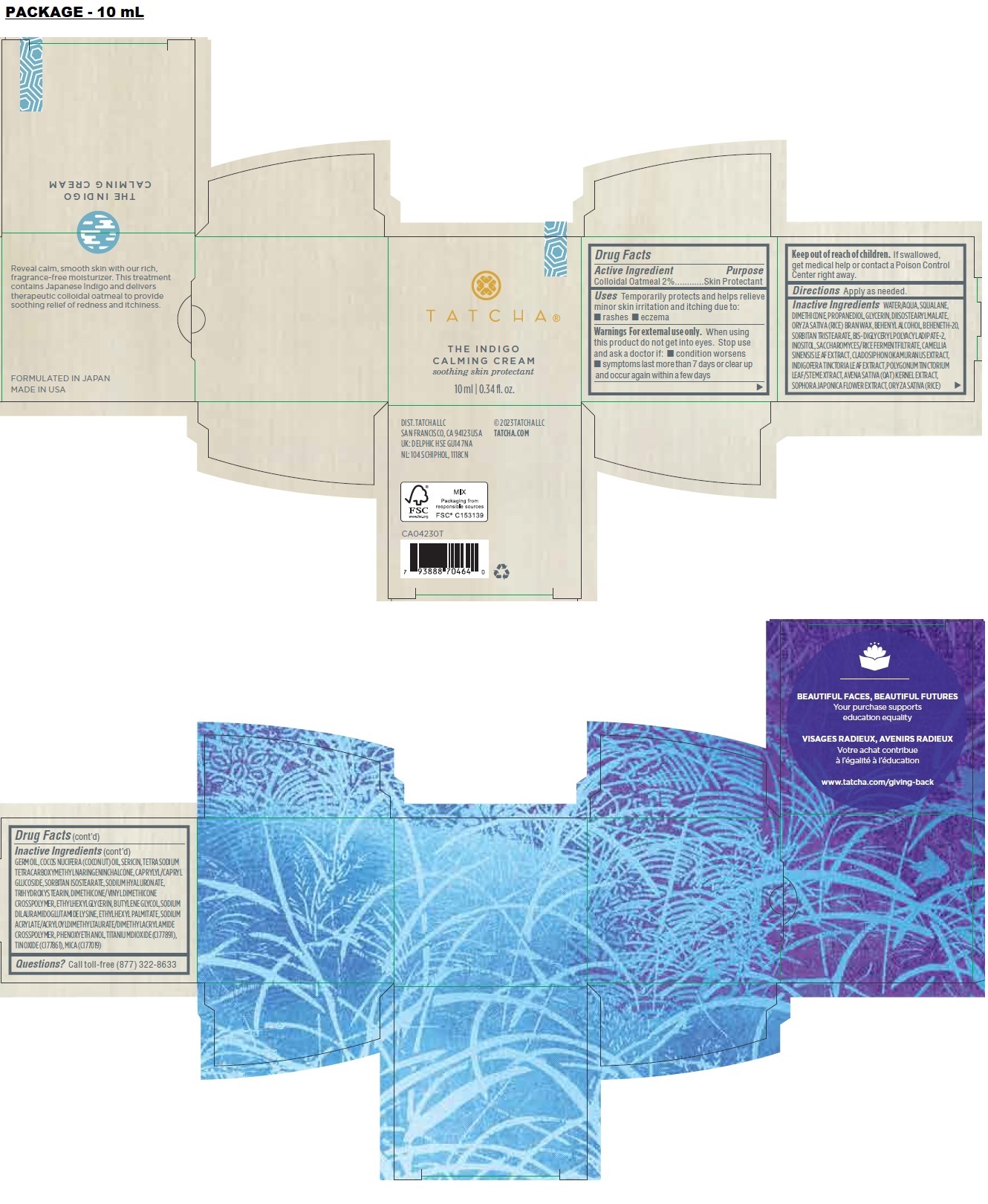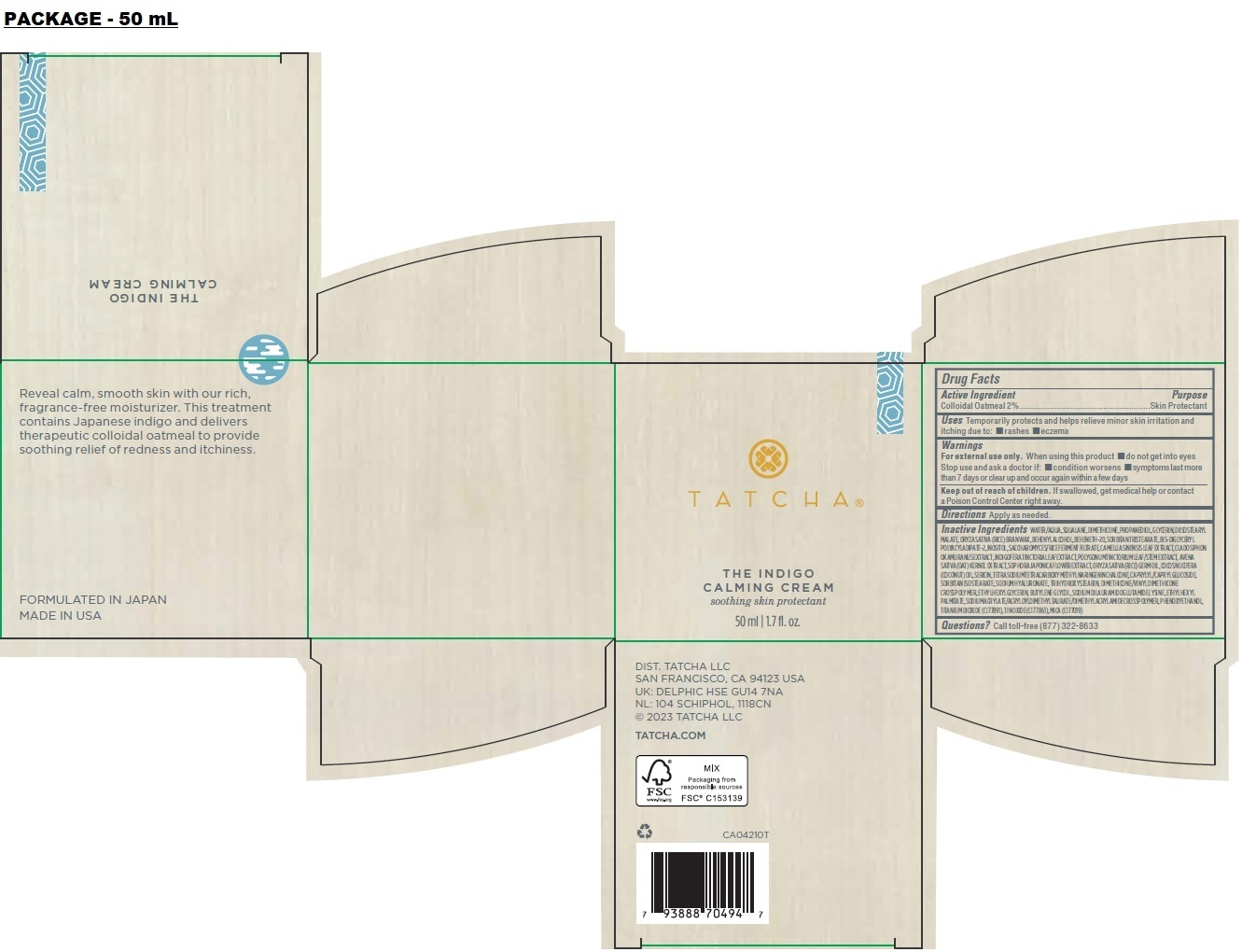 DRUG LABEL: THE INDIGO CALMING
NDC: 69417-140 | Form: CREAM
Manufacturer: TATCHA INC.
Category: otc | Type: HUMAN OTC DRUG LABEL
Date: 20250331

ACTIVE INGREDIENTS: OATMEAL 20 mg/1 mL
INACTIVE INGREDIENTS: WATER; SQUALANE; DIMETHICONE, UNSPECIFIED; PROPANEDIOL; GLYCERIN; DIISOSTEARYL MALATE; RICE BRAN; BEHENETH-20; SORBITAN TRISTEARATE; BIS-DIGLYCERYL POLYACYLADIPATE-2; INOSITOL; GREEN TEA LEAF; CLADOSIPHON OKAMURANUS WHOLE; INDIGO; OAT; STYPHNOLOBIUM JAPONICUM FLOWER; RICE GERM OIL; COCONUT OIL; SILK SERICIN; CAPRYLYL/CAPRYL OLIGOGLUCOSIDE; SORBITAN ISOSTEARATE; HYALURONATE SODIUM; TRIHYDROXYSTEARIN; DIMETHICONE/VINYL DIMETHICONE CROSSPOLYMER (SOFT PARTICLE); ETHYLHEXYLGLYCERIN; BUTYLENE GLYCOL; SODIUM DILAURAMIDOGLUTAMIDE LYSINE; ETHYLHEXYL PALMITATE; PHENOXYETHANOL; TITANIUM DIOXIDE; STANNIC OXIDE; MICA

TATCHA® THE INDIGO CALMING CREAM

Active Ingredient

Colloidal Oatmeal 2%

Purpose

Skin Protectant

Uses

Temporarily protects and helps relieve minor skin irritation and itching due to: • rashes • eczema

Warnings

For external use only. When using this product do not get into eyes. Stop use and ask a doctor if: • condition worsens • symptoms last more than 7 days or clear up and occur again within a few days

Keep out of reach of children. If swallowed, get medical help or contact a Poison Control Center right away.

Directions

Apply as needed.

Inactive Ingredients

Water/Aqua, Squalane, Dimethicone, Propanediol, Glycerin, Diisostearyl Malate, Oryza Sativa (Rice) Bran Wax, Behenyl Alcohol, Beheneth-20, Sorbitan Tristearate, Bis-Diglyceryl Polyacyladipate-2, Inositol, Saccharomyces/Rice Ferment Filtrate, Camellia Sinensis Leaf Extract, Cladosiphon Okamuranus Extract, Indigofera Tinctoria Leaf Extract, Polygonum Tinctorium Leaf/Stem Extract, Avena Sativa (Oat) Kernel Extract, Sophora Japonica Flower Extract, Oryza Sativa (Rice) Germ Oil, Cocos Nucifera (Coconut) Oil, Sericin, Tetrasodium Tetracarboxymethyl Naringeninchalcone, Caprylyl/Capryl Glucoside, Sorbitan Isostearate, Sodium Hyaluronate, Trihydroxystearin, Dimethicone/Vinyl Dimethicone Crosspolymer, Ethylhexylglycerin, Butylene Glycol, Sodium Dilauramidoglutamide Lysine, Ethylhexyl Palmitate, Sodium Acrylate/ Acryloyldimethyltaurate/Dimethylacrylamide Crosspolymer, Phenoxyethanol, Titanium Dioxide (CI 77891), Tin Oxide (CI 77861), Mica (CI 77019)

Questions?

Call toll-free (877) 322-8633

soothing skin protectant

Reveal calm, smooth skin with our rich, fragrance-free moisturizer. This treatment contains Japanese indigo and delivers therapeutic colloidal oatmeal to provide soothing relief of redness and itchiness.

FORMULATED IN JAPAN
MADE IN THE USA OF INTERNATIONAL INGREDIENTS

DIST. TATCHA LLC
SAN FRANCISCO, CA 94123 USA
UK: DELPHIC HSE GU14 7NA
NL: 104 SCHIPHOL, 1118CN

© 2025 TATCHA LLC
QUESTIONS@TATCHA.COM

BEAUTIFUL FACES, BEAUTIFUL FUTURES

Every Tatcha purchase supports education equality worldwide.

www.tatcha.com/giving-back